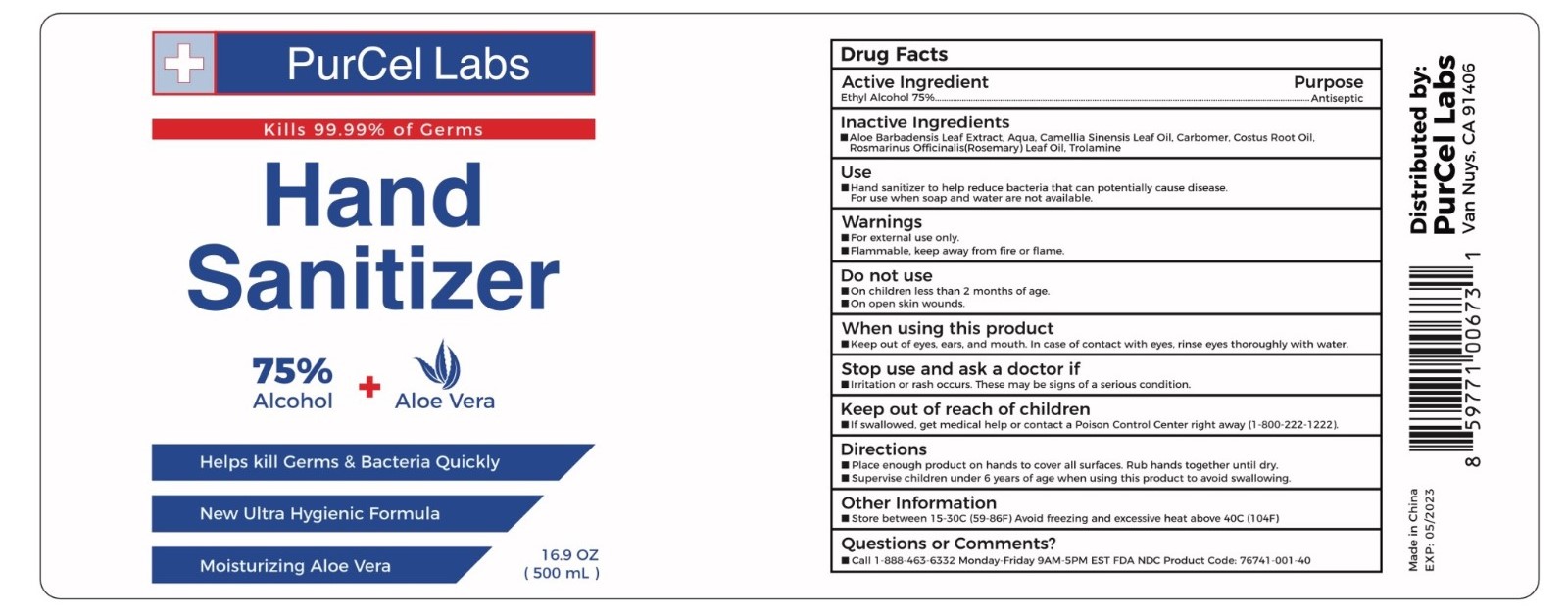 DRUG LABEL: Hand Sanitizer
NDC: 76741-001 | Form: GEL
Manufacturer: Sutra Beauty Inc
Category: otc | Type: HUMAN OTC DRUG LABEL
Date: 20201230

ACTIVE INGREDIENTS: ALCOHOL 75 mL/100 mL
INACTIVE INGREDIENTS: TEA LEAF OIL 0.1 mL/100 mL; CARBOMER 940 0.75 mL/100 mL; TROLAMINE 0.25 mL/100 mL; ROSEMARY OIL 0.1 mL/100 mL; COSTUS ROOT OIL 0.2 mL/100 mL; ALOE VERA LEAF 0.2 mL/100 mL; WATER 22.4 mL/100 mL

Hand Sanitizer

Active Ingredient(s)

Ethyl Alcohol 75% Purpose: Antiseptic

Inactive ingredients

Aloe Barbadensis Leaf Extract, Aqua, Camellia Sinensis Leaf Oil, Carbomer, Costus Root Oil, Rosmarinus Officinalis (Rosemary) Leaf Oil, Trolamine

Purpose

Antiseptic, Hand Sanitizer

Use

Hand Sanitizer to help reduce bacteria that potentially can cause disease. For use when soap and water are not available.

Warnings

For external use only. Flammable. Keep away from heat or flame

Do not use

- in children less than 2 months of age
- on open skin wounds

When using this product keep out of eyes, ears, and mouth. In case of contact with eyes, rinse eyes thoroughly with water.
Stop use and ask a doctor if irritation or rash occurs. These may be signs of a serious condition.
Keep out of reach of children. If swallowed, get medical help or contact a Poison Control Center right away.

Stop use and ask a doctor if irritation or rash occurs. These may be signs of a serious condition.

Keep out of reach of children. If swallowed, get medical help or contact a Poison Control Center right away.

Directions

- Place enough product on hands to cover all surfaces. Rub hands together until dry.
- Supervise children under 6 years of age when using this product to avoid swallowing.

Other information

- Store between 15-30C (59-86F)
- Avoid freezing and excessive heat above 40C (104F)

Package Label - Principal Display Panel

500 ml NDC: 76741-001-40